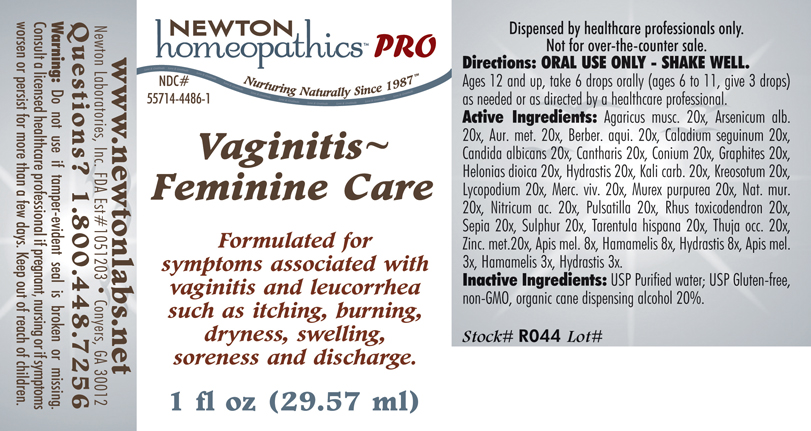 DRUG LABEL: Vaginitis - Feminine Care 
NDC: 55714-4486 | Form: LIQUID
Manufacturer: Newton Laboratories, Inc.
Category: homeopathic | Type: HUMAN PRESCRIPTION DRUG LABEL
Date: 20110601

ACTIVE INGREDIENTS: Amanita Muscaria Var. Muscaria Fruiting Body 20 [hp_X]/1 mL; Arsenic Trioxide 20 [hp_X]/1 mL; Gold 20 [hp_X]/1 mL; Mahonia Aquifolium Root Bark 20 [hp_X]/1 mL; Dieffenbachia Seguine 20 [hp_X]/1 mL; Candida Albicans 20 [hp_X]/1 mL; Lytta Vesicatoria 20 [hp_X]/1 mL; Conium Maculatum Flowering Top 20 [hp_X]/1 mL; Graphite 20 [hp_X]/1 mL; Chamaelirium Luteum Root 20 [hp_X]/1 mL; Goldenseal 20 [hp_X]/1 mL; Potassium Carbonate 20 [hp_X]/1 mL; Wood Creosote 20 [hp_X]/1 mL; Lycopodium Clavatum Spore 20 [hp_X]/1 mL; Mercury 20 [hp_X]/1 mL; Sodium Chloride 20 [hp_X]/1 mL; Nitric Acid 20 [hp_X]/1 mL; Pulsatilla Vulgaris 20 [hp_X]/1 mL; Toxicodendron Pubescens Leaf 20 [hp_X]/1 mL; Sepia Officinalis Juice 20 [hp_X]/1 mL; Sulfur 20 [hp_X]/1 mL; Lycosa Tarantula 20 [hp_X]/1 mL; Thuja Occidentalis Leafy Twig 20 [hp_X]/1 mL; Zinc 20 [hp_X]/1 mL; Apis Mellifera 8 [hp_X]/1 mL; Hamamelis Virginiana Root Bark/stem Bark 8 [hp_X]/1 mL; Hexaplex Trunculus Hypobranchial Gland Juice 20 [hp_X]/1 mL
INACTIVE INGREDIENTS: Alcohol

Vaginitis - Feminine Care

INDICATIONS & USAGE SECTION

Vaginitis - Feminine Care Formulated for symptoms associated with vaginitis and leucorrhea such as itching, burning, dryness, swelling, snoreness and discharge.

DOSAGE & ADMINISTRATION SECTION

Directions: ORAL USE ONLY - SHAKE WELL. Ages 12 and up, take 6 drops orally (ages 6 to 11, give 3 drops) as needed or as directed by a healthcare professional.

ACTIVE INGREDIENT SECTION

Agaricus musc. 20x, Arsenicum alb. 20x, Aur. met. 20x, Berber. aqui. 20x, Caladium seguinum 20x, Candida albicans 20x, Cantharis 20x, Conium 20x, Graphites 20x, Helonias dioica 20x, Hydrastis 20x, Kali carb. 20x, Kreosotum 20x, Lycopodium 20x, Merc. viv. 20x, Murex purpurea 20x, Nat. mur. 20x, Nitricum ac. 20x, Pulsatilla 20x, Rhus toxicodendron 20x, Sepia 20x, Sulphur 20x, Tarentula hispana 20x, Thuja occ. 20x, Zinc. met. 20x, Apis mel. 8x, Hamamelis 8x, Hydrastis 8x, Apis mel. 3x, Hamamelis 3x, Hydrastis 3x.

PURPOSE SECTION

Formulated for symptoms associated with vaginitis and leucorrhea such as itching, burning, dryness, swelling, snoreness and discharge.

INACTIVE INGREDIENT SECTION

Inactive Ingredients: USP Purified Water; USP Gluten-free, non-GMO, organic cane dispensing alcohol 20%.

QUESTIONS? SECTION

www.newtonlabs.net Newton Laboratories, Inc. FDA Est # 1051203 - Conyers, GA 30012
Questions? 1.800.448.7256

WARNINGS SECTION

Warning: Do not use if tamper - evident seal is broken or missing. Consult a licensed healthcare professional if pregnant, nursing or if symptoms worsen or persist for more than a few days. Keep out of reach of children.

PREGNANCY OR BREAST FEEDING SECTION

Consult a licensed healthcare professional if pregnant, nursing or if symptoms worsen or persist for more than a few days.

KEEP OUT OF REACH OF CHILDREN SECTION

Keep out of reach of children.